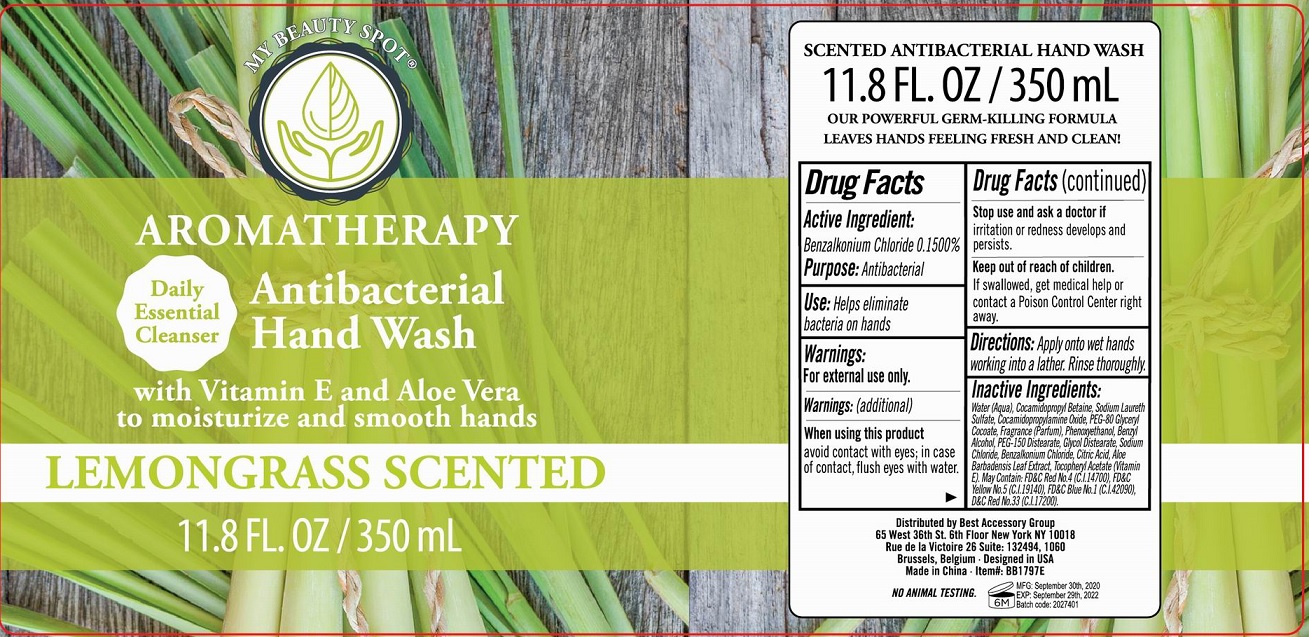 DRUG LABEL: Aromatherapy Antibacterial Hand Wash Lemongrass Scented
NDC: 56136-472 | Form: GEL
Manufacturer: Ganzhou Olivee Cosmetic Co., Ltd.
Category: otc | Type: HUMAN OTC DRUG LABEL
Date: 20201112

ACTIVE INGREDIENTS: BENZALKONIUM CHLORIDE 1.5 mg/1 mL
INACTIVE INGREDIENTS: WATER; COCAMIDOPROPYL BETAINE; COCAMIDOPROPYLAMINE OXIDE; BENZYL ALCOHOL; GLYCERIN; ACETYLTRIETHYL CITRATE; PHENOXYETHANOL; .ALPHA.-TOCOPHEROL ACETATE, D-; FD&C RED NO. 4; FD&C BLUE NO. 1; FD&C YELLOW NO. 5

Hand Wash

Active ingredient

Benzalkonium Chloride 0.15%

Purpose

Antibacterial

Use

Helps eliminate bacteria on hands

Warnings

For external use only.

When using this product

avoi contact with eyes; in case of contact, flush eyes with water.

Stop use and ask a doctor if

- irritation and redness develops and persists.

Keep out of reach of children.

If swallowed, get medical help or contact a Poison Control Center right away.

Directions

Apply onto wet hands working into a lather. Rinse thorougly.

Inactive ingredients

Water (Aqua), Cocamidopropyl Betaine, Cocamidopropylamine Oxide, Hydroxethylcellulose, Fragrance (Parfum), Phenoxyethanol, Bezyl Alcohol, Glycerin, Citric Acid, Tocopheryl Acetate, Aloe Barbadensis Leaf Extract, D&C Red No. 33 (Cl 17200), FD&C Blue No. 1 (Cl 42090).